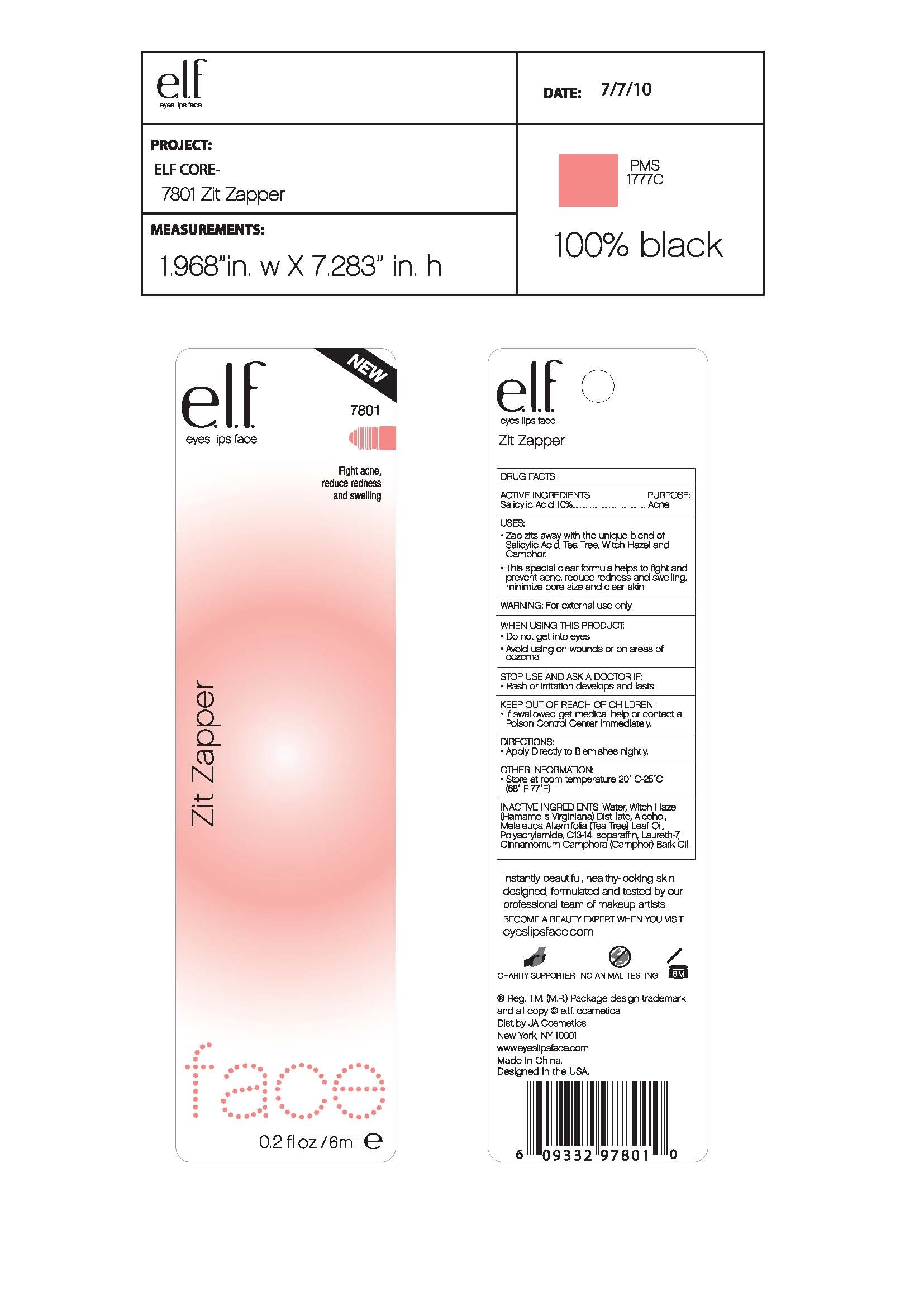 DRUG LABEL: ELF Zit Zapper
NDC: 52664-007 | Form: LIQUID
Manufacturer: Hangzhou Facecare Cosmetics Co., Ltd.
Category: otc | Type: HUMAN OTC DRUG LABEL
Date: 20101117

ACTIVE INGREDIENTS: SALICYLIC ACID 1.0 g/100 g
INACTIVE INGREDIENTS: WATER 86.70 g/100 g; HAMAMELIS VIRGINIANA LEAF; ALCOHOL; TEA TREE OIL; C13-14 ISOPARAFFIN; LAURETH-7; CAMPHOR OIL

Drug Fact

Active Ingredient:

Salicylic Acid 1.0%

Purpose:

Acne

Uses:

- Zap zits away with the unique blend of Salicylic Acid, Tea Tree, Witch Hazel, and Camphor
- The special clear formula helps to fight and prevent acne, reduce redness and swelling, minimize pore size and clear skin

Warning:

For external use only

When Using This Product:

Do not get into eyes

Avoid using on wounds or on areas of eczema

Stop Use and Ask A Doctor If:

Rash or irritation develops and lasts

Keep Out of Reach of Children:

If swallowed get medical help or contact a Poison Control Center immediately

Directions:

Apply directly to blemishes nightly

Other Information:

Store at room temperature 20-25C (68-77F)

Inactive Ingredient:

Water, Witch Hazel (Hamamelis Virginiana) Distillate, Alcohol, Melaleuca Alternifolia (Tea Tree) Leaf Oil, Polyacrylamide, C13-14 Isoparaffin, Laureth-7, Cinnamomum Camphora (Camphor) Bark Oil

PACKAGE LABEL

labe